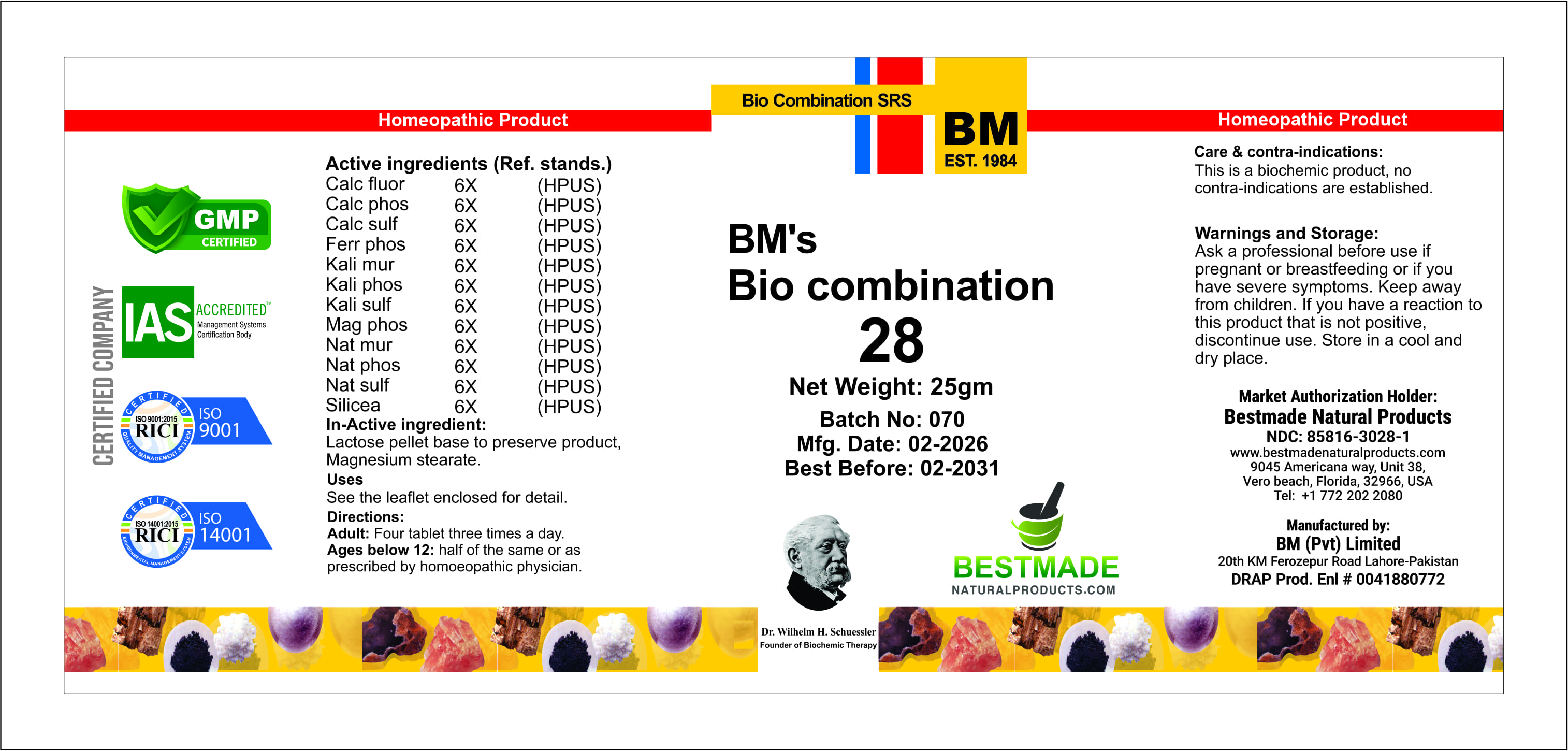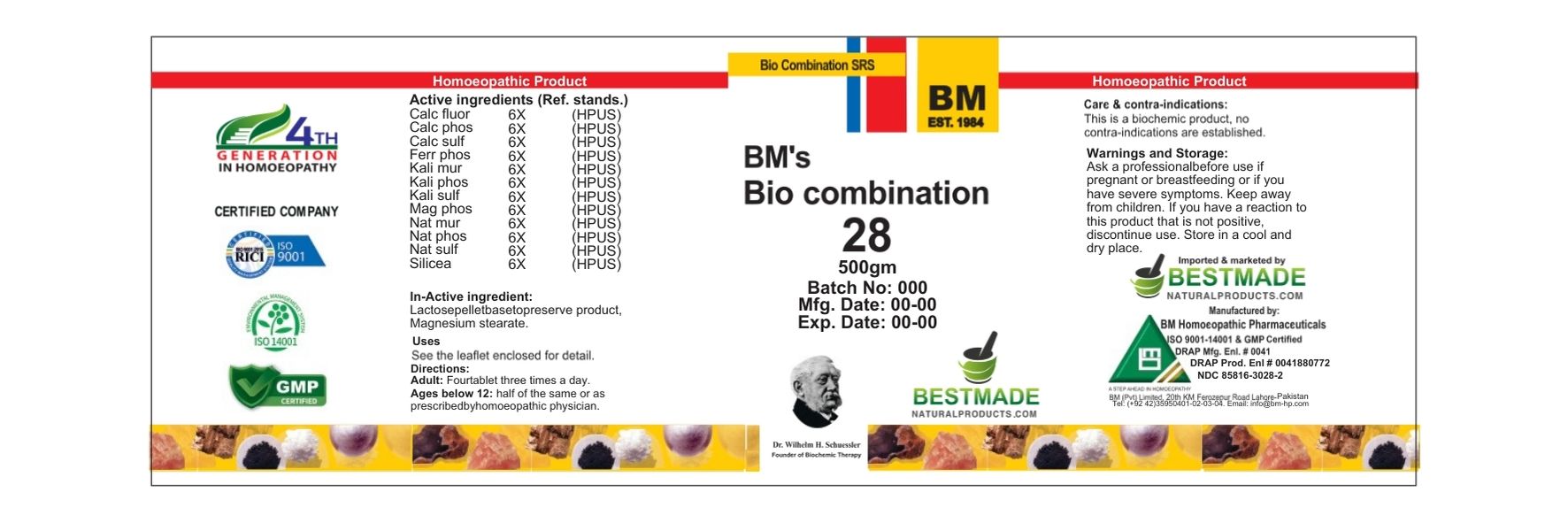 DRUG LABEL: BM BIO28 (General Tonic)
NDC: 85816-3028 | Form: GLOBULE
Manufacturer: BM Private Limited
Category: homeopathic | Type: HUMAN OTC DRUG LABEL
Date: 20260223

ACTIVE INGREDIENTS: TRIBASIC CALCIUM PHOSPHATE 6 [hp_X]/1 g; POTASSIUM CHLORIDE 6 [hp_X]/1 g; SILICON DIOXIDE 6 [hp_X]/1 g; CALCIUM FLUORIDE 6 [hp_X]/1 g; SODIUM SULFATE 6 [hp_X]/1 g; MAGNESIUM PHOSPHATE, DIBASIC TRIHYDRATE 6 [hp_X]/1 g; POTASSIUM SULFATE 6 [hp_X]/1 g; POTASSIUM PHOSPHATE, DIBASIC 6 [hp_X]/1 g; CALCIUM SULFATE ANHYDROUS 6 [hp_X]/1 g; FERROSOFERRIC PHOSPHATE 6 [hp_X]/1 g; SODIUM PHOSPHATE, DIBASIC, HEPTAHYDRATE 6 [hp_X]/1 g; SODIUM CHLORIDE 6 [hp_X]/1 g
INACTIVE INGREDIENTS: LACTOSE, UNSPECIFIED FORM 0.978 g/1 g; MAGNESIUM STEARATE 0.0208 g/1 g

BM BIO 28 (General Tonic)

Indications: See the leaflet enclosed for detail.

DOSAGE AND ADMINISTRATION

Dosage: Adult: Four tablets three times a day, Children: half of the same or as advised by a homoeopathic physician.

PURPOSE

Indications: See the leaflet enclosed for detail.

WARNINGS

Precautions/storage: Keep away from children and store at cool and dry place.

KEEP OUT OF REACH OF CHILDREN

Precautions/storage: Keep away from children and store at cool and dry place.

STORAGE AND HANDLING

Precautions/storage: Keep away from children and store at cool and dry place.

ACTIVE INGREDIENT

CALC SULPH, CALC FLUOR, CALC PHOS, FERR PHOS, KALI MUR, KALI PHOS, KALI SULPH, MAG PHOS, NAT PHOS, NAT SULPH, NAT MUR, SILICEA

INACTIVE INGREDIENT

LACTOSE, MAGNESIUM STEARATE

Package 1 (30g)

Package 2 (500g)